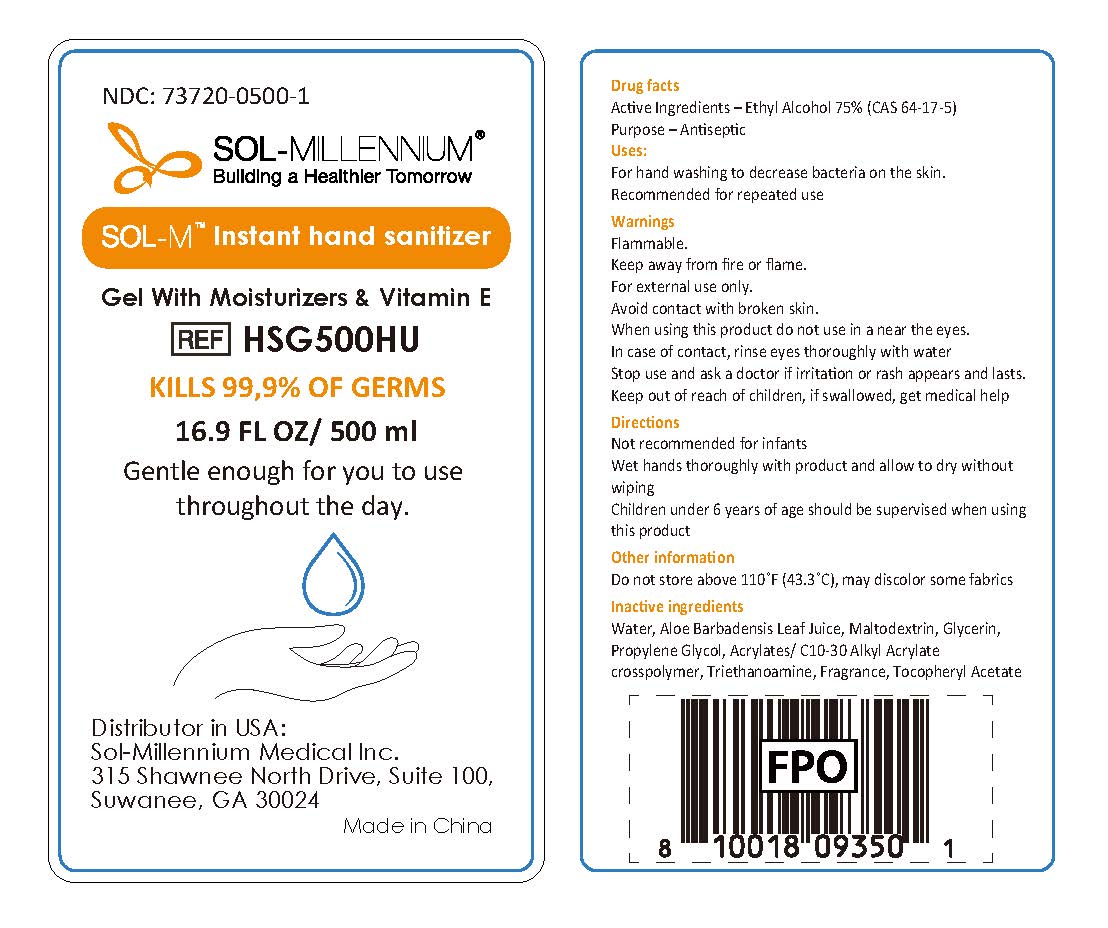 DRUG LABEL: Sol-M Instant Hand Sanitizer
NDC: 73720-0500 | Form: GEL
Manufacturer: Sol-Millennium Medical Inc
Category: otc | Type: HUMAN OTC DRUG LABEL
Date: 20200811

ACTIVE INGREDIENTS: ALCOHOL 75 mL/100 mL
INACTIVE INGREDIENTS: PROPYLENE GLYCOL; ALOE VERA LEAF; MALTODEXTRIN; WATER; TROLAMINE; GLYCERIN; CARBOMER INTERPOLYMER TYPE A (55000 CPS); .ALPHA.-TOCOPHEROL ACETATE

Sol-Millennium Hand Sanitizer

Active Ingredient(s)

Ethyl Alcohol 75%

Purpose

Antiseptic

Use

For hand washing to decrease bacteria on the skin.
Recommended for repeated use

Warnings

Flammable.

Keep away from heat or flame.

For external use only.

WHEN USING

Avoid contact with broken skin.
When using this product do not use in a near the eyes.
In case of contact, rinse eyes thoroughly with water.

Stop use and ask a doctor if irritation or rash appears and lasts.

Keep out of reach of children, if swallowed, get medical help

Directions

Not recommended for infants
Wet hands thoroughly with product and allow to dry without wiping
Children under 6 years of age should be supervised when using this product

Other information

Do not store above 110˚F (43.3˚C), may discolor some fabrics

Inactive ingredients

Water, Aloe Barbadensis Leaf Juice, Maltodextrin, Glycerin, Propylene Glycol, Acrylates/ C10-30 Alkyl Acrylate crosspolymer, Triethanoamine, Fragrance, Tocopheryl Acetate